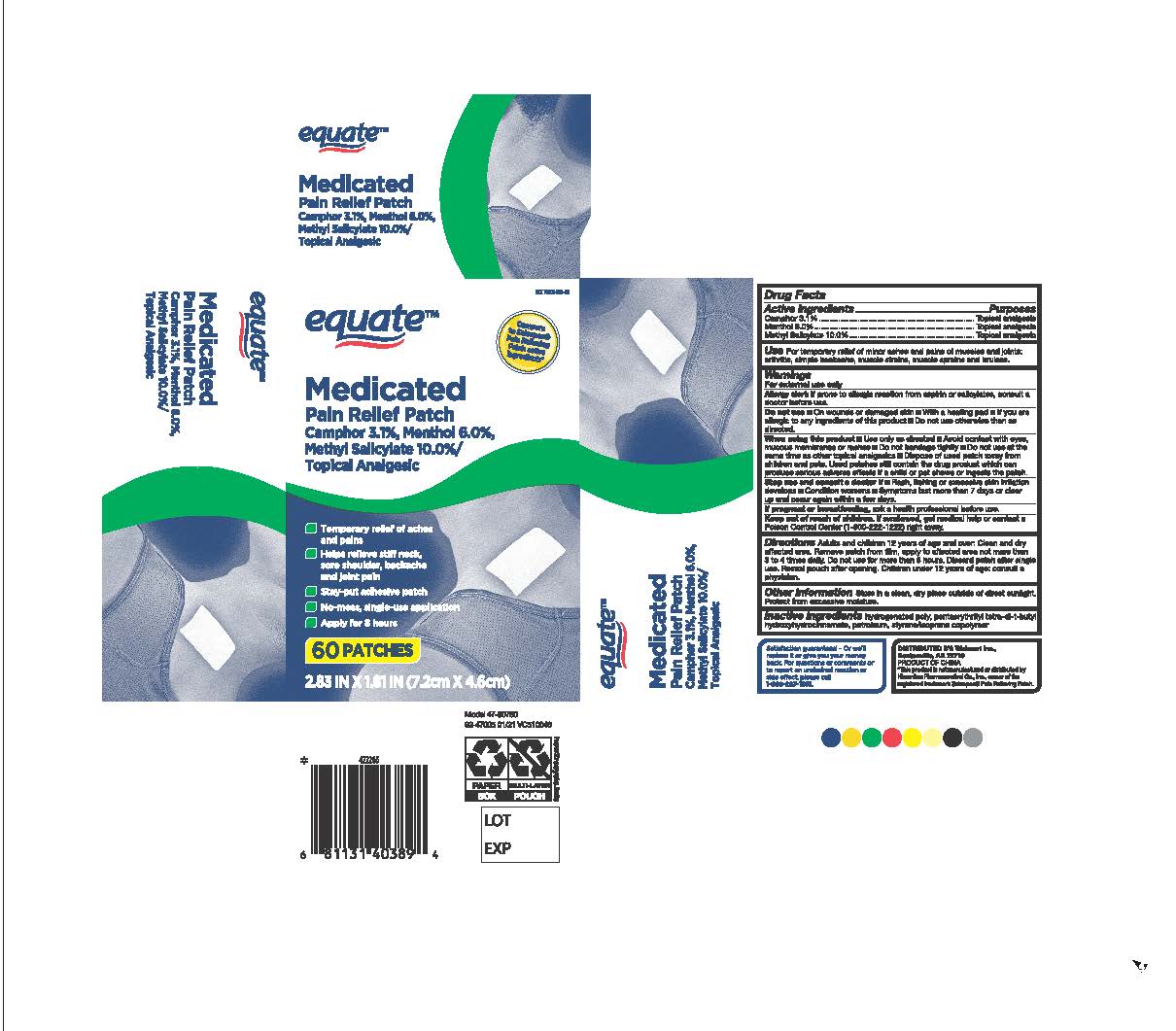 DRUG LABEL: Equate Pain Relief Patch Camphor/Menthol/Salicylate
NDC: 79903-039 | Form: PATCH
Manufacturer: Walmart Stores Inc
Category: otc | Type: HUMAN OTC DRUG LABEL
Date: 20260129

ACTIVE INGREDIENTS: CAMPHOR (SYNTHETIC) 3.1 g/100 g; MENTHOL 6 g/100 g; METHYL SALICYLATE 10 g/100 g
INACTIVE INGREDIENTS: LIQUID PETROLEUM; PENTAERYTHRITOL TETRAKIS(3-(3,5-DI-TERT-BUTYL-4-HYDROXYPHENYL)PROPIONATE); STYRENE/ACRYLAMIDE COPOLYMER (MW 500000); HYDROGENATED POLYDECENE TYPE I

Equate Pain Relief Patch Camphor/Menthol/Salicylate 60 ct

Active ingredients

Camphor 3.1%

Menthol 6.0%

Methyl salicylate 10.0%

Purpose

Topical analgesic

Uses

For temporary relief of minor aches and pains of muscles and joints associated with:

- arthritis
- simple backache
- muscle strains
- muscle sprains and bruises

Warnings

For external use only

Allergy alert:

If prone to allergic reaction from aspirin or salicylates, consult a doctor before use.

Do not use

- on wounds or damaged skin
- with a heating pad
- if you are allergic to any ingredients of this product
- Do not use otherwise than as directed

When using this product

- use only as directed
- avoid contact with the eyes, mucous membranes, or rashes
- do not bandage tightly
- Do not use at the same time as other topical analgesics
- Dispose of used patch away from children and pets. Used patches still contain the drug product that can produce serious adverse effects if a child or pet chews or ingests this patch.

Stop use and ask a doctor if

- rash, itching, or excessive skin irritation develops
- conditions worsen
- symptoms last for more than 7 days or clear up and occur again within a few days

If pregnant or breast-feeding,

ask a health professional before use.

Keep out of reach of children.

If swallowed, get medical help or contact a Poison Control Center (1-800-222-1222) right away.

Directions

Adults and children 12 years of age and over:

- clean and dry affected area
- remove patch from film
- apply to affected area not more than 3 to 4 times daily
- Do not use for more than 8 hours.
- Discard patch after single use. Reseal pouch after opening.

Children under 12 years of age: consult a doctor

Other information

Store in a clean, dry place outside of direct sunlight. Protect for excessive moisture.

Inactive ingredients

hydrogenated poly, pentaerythrityl tetra-di-t-butyl hydroxyhydrocinnamate, petroleum, styrene/isoprene copolymer.